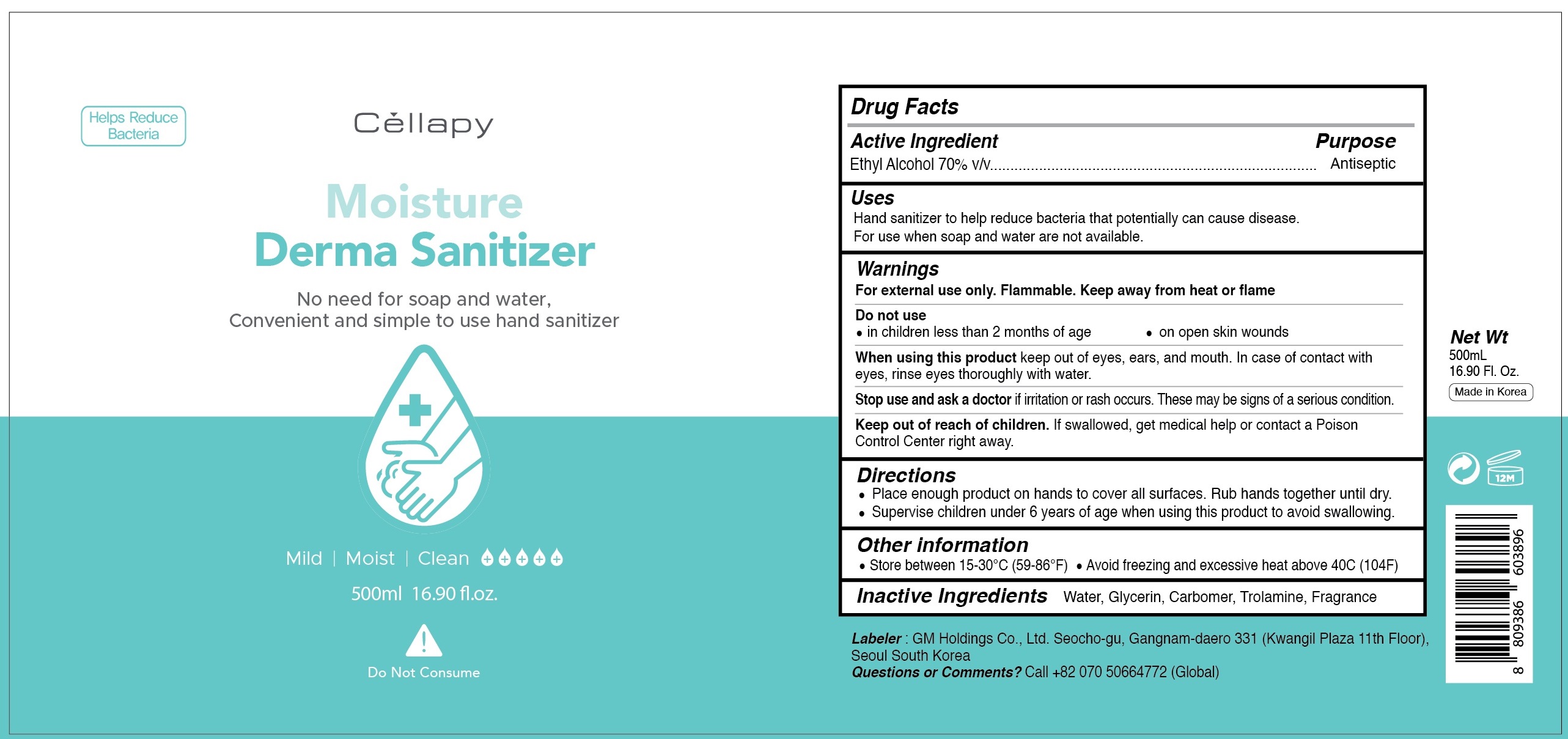 DRUG LABEL: Cellapy Derma Moisture Sanitizer
NDC: 69278-117 | Form: GEL
Manufacturer: GM Holdings Co., Ltd
Category: otc | Type: HUMAN OTC DRUG LABEL
Date: 20200515

ACTIVE INGREDIENTS: ALCOHOL 350 mL/500 mL
INACTIVE INGREDIENTS: Water; GLYCERIN; CARBOMER HOMOPOLYMER, UNSPECIFIED TYPE; Trolamine

Drug Facts

ACTIVE INGREDIENT

Ethyl Alcohol 70% v/v

INACTIVE INGREDIENTS

Water, Glycerin, Carbomer, Trolamine, Fragrance

PURPOSE

Antiseptic

WARNINGS

For external use only. Flammable. Keep away from heat or flame

Do not use
• in children less than 2 months of age
• on open skin wounds

When using this product keep out of eyes, ears, and mouth. In case of contact with eyes, rinse eyes thoroughly with water.

Stop use and ask a doctor if irritation or rash occurs. These may be signs of a serious condition.

KEEP OUT OF REACH OF CHILDREN

If swallowed, get medical help or contact a Poison Control Center right away.

Uses:

Hand sanitizer to help reduce bacteria that potentially can cause disease.

For use when soap and water are not available

Directions

• Place enough product on hands to cover all surfaces. Rub hands together until dry.
• Supervise children under 6 years of age when using this product to avoid swallowing.

Other information

• Store between 15-30C (59-86F)
• Avoid freezing and excessive heat above 40C (104F)